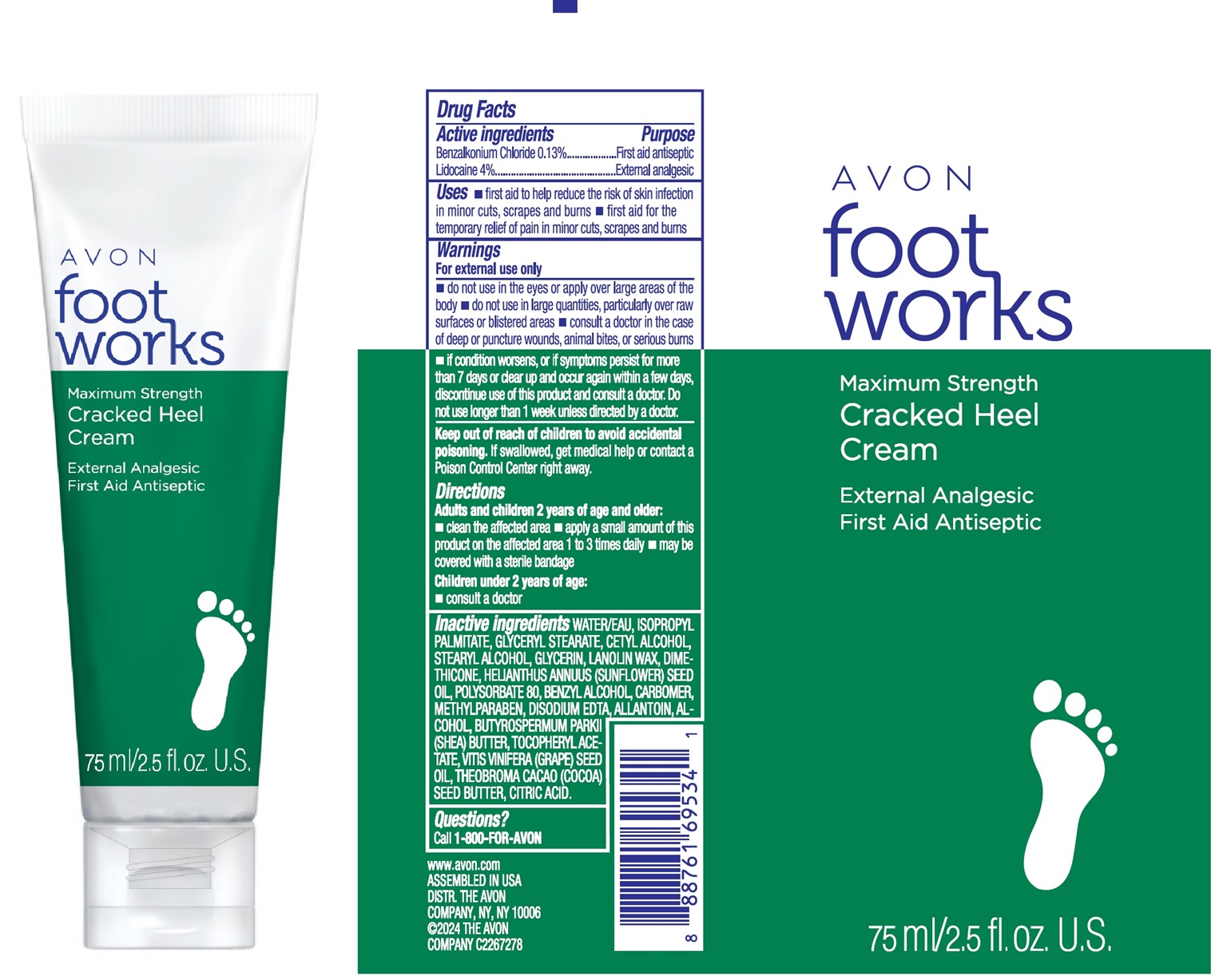 DRUG LABEL: FOOT WORKS MAXIMUM CRACKED HEEL
NDC: 68577-195 | Form: CREAM
Manufacturer: COSMAX USA, CORPORATION
Category: otc | Type: HUMAN OTC DRUG LABEL
Date: 20241223

ACTIVE INGREDIENTS: BENZALKONIUM CHLORIDE 1.3 mg/1 mL; LIDOCAINE 40 mg/1 mL
INACTIVE INGREDIENTS: EDETATE DISODIUM; ALLANTOIN; CITRIC ACID; STEARYL ALCOHOL; GLYCERYL STEARATE; .ALPHA.-TOCOPHEROL ACETATE; ISOPROPYL PALMITATE; CETYL ALCOHOL; HELIANTHUS ANNUUS (SUNFLOWER) SEED OIL; BENZYL ALCOHOL; ALCOHOL; VITIS VINIFERA (GRAPE) SEED OIL; GLYCERIN; THEOBROMA CACAO (COCOA) SEED BUTTER; WATER; DIMETHICONE; POLYSORBATE 80; METHYLPARABEN; BUTYROSPERMUM PARKII (SHEA) BUTTER

AVON FOOTWORKS MAXIMUM STRENGTH CRACKED HEEL

Active Ingredients

Benzalkonium Chloride 0.13%

Lidocaine 4%

Purpose

First aid antiseptic

External analgesic

USES

- first aid to help reduce the risk of skin infection in minor cuts, scrapes and burns
- first aid for the temporary reflief of pain in minor cuts, scrapes and burns

Warnings

For external use only

- do not use in the eyes or apply over large areas of the body
- do not use in large quantities, particularly over raw surfaces or blistered areas
- consult a doctor in the case of deep or puncture wounds, animal bites, or serious burns
- if condition worsens, of if symptoms persist for more than 7 days or clear up and occur again within a few days, discontinue use of this product and consult a doctor. Do not use longer than 1 week unless directed by a doctor

Keep out of reach of children to avoid accidental poisoning. If swallowed, get medical help or contact a Poison Control Center right away.

DIRECTIONS

Adults and children 2 years of age and older

- clean the affected area
- apply a small amount of this product on the affected are 1 to 3 times daily
- may be covered with a sterile bandage

Children under 2 years of age

- consult a doctor

Inactive Ingredients:

Water, Isopropyl Palmitate, Glyceryl Stearate, Cetyl Alcohol, Stearyl Alcohol, Glycerin, Lanolin Wax, Dimethicone, Helianthus Annuus (Sunflower) Seed Oil, Polysorbate 80, Benzyl Alcohol, Carbomer, Methylparaben, Disodium EDTA, Allantoin, Alcohol, Butyrospermum Parkii (Shea) Butter, Tocopheryl Acetate, Vitis Vinifera (Grape) Seed Oil, Theobroma Cacao (Cocoa) Seed Butter, Citric Acid